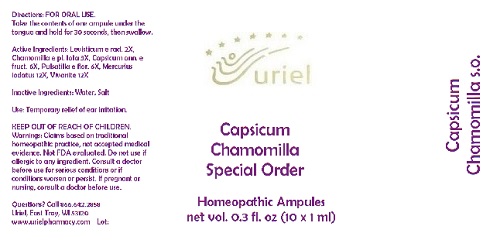 DRUG LABEL: Capsicum Chamomilla Special Order
NDC: 48951-3018 | Form: LIQUID
Manufacturer: Uriel Pharmacy Inc.
Category: homeopathic | Type: HUMAN OTC DRUG LABEL
Date: 20170731

ACTIVE INGREDIENTS: LEVISTICUM OFFICINALE ROOT 2 [hp_X]/1 mL; MATRICARIA RECUTITA 3 [hp_X]/1 mL; PAPRIKA 6 [hp_X]/1 mL; PULSATILLA VULGARIS 6 [hp_X]/1 mL; MERCURIC IODIDE 12 [hp_X]/1 mL; FERROSOFERRIC PHOSPHATE 12 [hp_X]/1 mL
INACTIVE INGREDIENTS: WATER; SODIUM CHLORIDE

Capsicum Chamomilla Special Order

INDICATIONS AND USAGE

Directions: FOR ORAL USE.

DOSAGE AND ADMINISTRATION

Take the contents of one ampule under the tongue and hold for 30 seconds, then swallow.

ACTIVE INGREDIENT

Active Ingredients: Levisticum e rad. 2X, Chamomilla e pl. tota 3X, Capsicum ann. e fruct. 6X, Pulsatilla e flor. 6X, Mercurius iodatus 12X, Vivanite 12X

Inactive Ingredients: Water, Salt

PURPOSE

Use: Temporary relief of ear irritation.

KEEP OUT OF REACH OF CHILDREN.

WARNINGS

Warnings: Claims based on traditional homeopathic practice, not accepted medical evidence. Not FDA evaluated. Do not use if allergic to any ingredient. Consult a doctor before use for serious conditions or if conditions worsen or persist. If pregnant or nursing, consult a doctor before use.

QUESTIONS

Questions? Call 866.642.2858 Uriel, East Troy, WI 53120 www.urielpharmacy.com